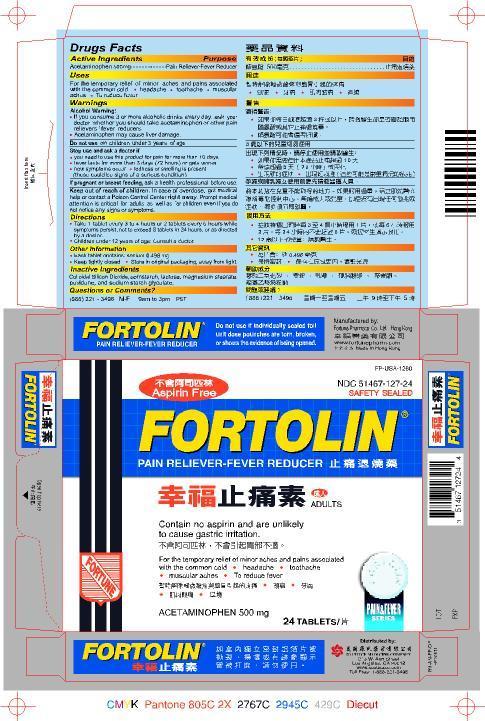 DRUG LABEL: FORTOLIN
NDC: 51467-127 | Form: TABLET
Manufacturer: FORTUNE PHARMACAL COMPANY, LIMITED
Category: otc | Type: HUMAN OTC DRUG LABEL
Date: 20140623

ACTIVE INGREDIENTS: ACETAMINOPHEN 500 mg/1 1
INACTIVE INGREDIENTS: COLLOIDAL SILICON DIOXIDE; STARCH, CORN; LACTOSE; MAGNESIUM STEARATE; POVIDONE; SODIUM STARCH GLYCOLATE TYPE A POTATO

Drug Facts

Active ingredients
Acetaminophen 500 mg

Purpose
Pain reliever-fever reducer

Uses
For the temporary relief of minor aches and pains associated with the common cold
headache
toothache
muscular aches
To reduce fever

Warnings Alcohol warning:
If you consume 3 or more alcoholic drinks every day, ask your doctor whether you should take acetaminophen or otehr pain relievers/fever reducers.
Acetaminophen may cause liver damage

Do not use
on children under 3 years of age

Stop use and ask a doctor if
you need to use this product for pain for mroe than 10 days
fever lasts for more than 3 days (72 hours) or ets worse
new symptoms occur
redness or swelling is present (these could be signs of a serious condition)

PREGNANCY OR BREAST FEEDING

If pregnant or breast-feeding, ask a health professional before use.

Keep out of reach of children. In case of overdose, get medical help or contact a Poison Control Center right away.
Prompt medical attention is critical for adults as well as children even if you do not notice any signs or symptoms.

Directions
Take 1 tablet every 3 to 4 hours or 2 tablets every 6 hours while symptoms persist, not to exceed 8 tablets in 24 hours, or as directed by a doctor.
Children under 12 years of age : consult a docto

Other information
Each tablet contains sodium 0.496 mg
Keep tightly closed
Store in original packaging, away from sunlight

Inactive ingredients
colloidal silicon dioxide, corn starch, lactose, magnesium stearate, povidone, sodium starch glycolate

Questions or comments?
(888) 221-3496 M-F 9 am to 5 pm PST

PACKAGE LABEL

Fortolin

Pain Reliever Fever Reducer

NDC 51467-127-24

Aspirin Free

Contain no aspirin and are unlikely to cause gastric irritation.

Acetaminophen 500 mg

24 Tablets

Safety Sealed

Do not use if individually sealed foil unit dose pouches are torn, broken, or shows the evidence of being opened.